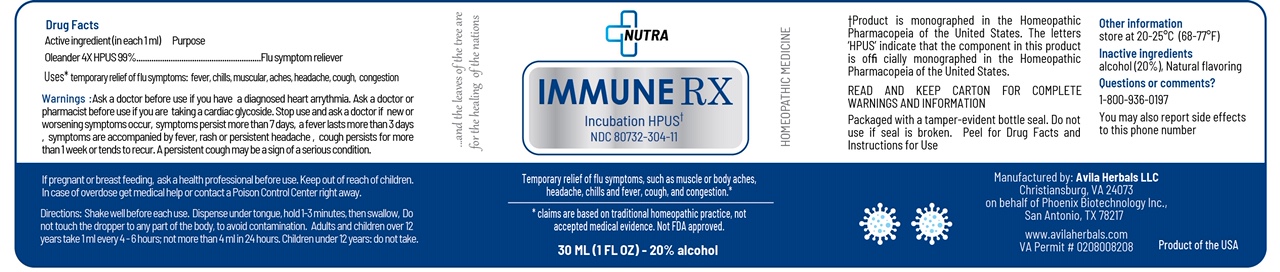 DRUG LABEL: ImmuneRX
NDC: 80732-305 | Form: TINCTURE
Manufacturer: Avila Herbals
Category: homeopathic | Type: HUMAN OTC DRUG LABEL
Date: 20220127

ACTIVE INGREDIENTS: NERIUM OLEANDER LEAF 4 [hp_X]/30 U
INACTIVE INGREDIENTS: ALCOHOL 6 U/30 U; WATER 23 U/30 U; ORANGE OIL TERPENELESS 0.9 mL/30 U

ImmuneRX

Immune RX

Oleander 4X HPUS

Purpose

Flu Symptom Reliever

INACTIVE INGREDIENT

Water, alcohol, orange oil terpeneless

INDICATIONS AND USAGE

Temporary relieft of flu symptoms: fever, chills, muscle aches, headache, cough, congestion

Ask a Doctor before use if you are:

experiencing worsening symptoms or if symptoms persist more than 7 days, have a diagnosed heart arrythmia, under 12 yrs.

When using this product

You may get drowsy

avoid alcoholic drinks

alcohol, sedatives, and tranquilizers may increase drowziness

be careful when driving a motor vehicle or operating machinery

If pregnant or breast-feeding, ask a health professional before use

Keep out of reach of chldren. In case of overdose, get medical help or contact posion Control Center right away

DOSAGE AND ADMINISTRATION

Shake well before use.

Dispense under tongue, hold 1-3 minutes, then swallow.

Adults and children over 12 years take 1 ml every 4-6 hours; not more than 4 ml in 24 hours.

Keep ptout of reach of children

DOSAGE AND ADMINISTRATION

take 1 ml up to 4 times per day not to exceed 4ml in 24 hrs

PACKAGE LABEL

NUTRA

ImmuneRX

HPUS

NDC 80732-305-11

Homeopathic medicine